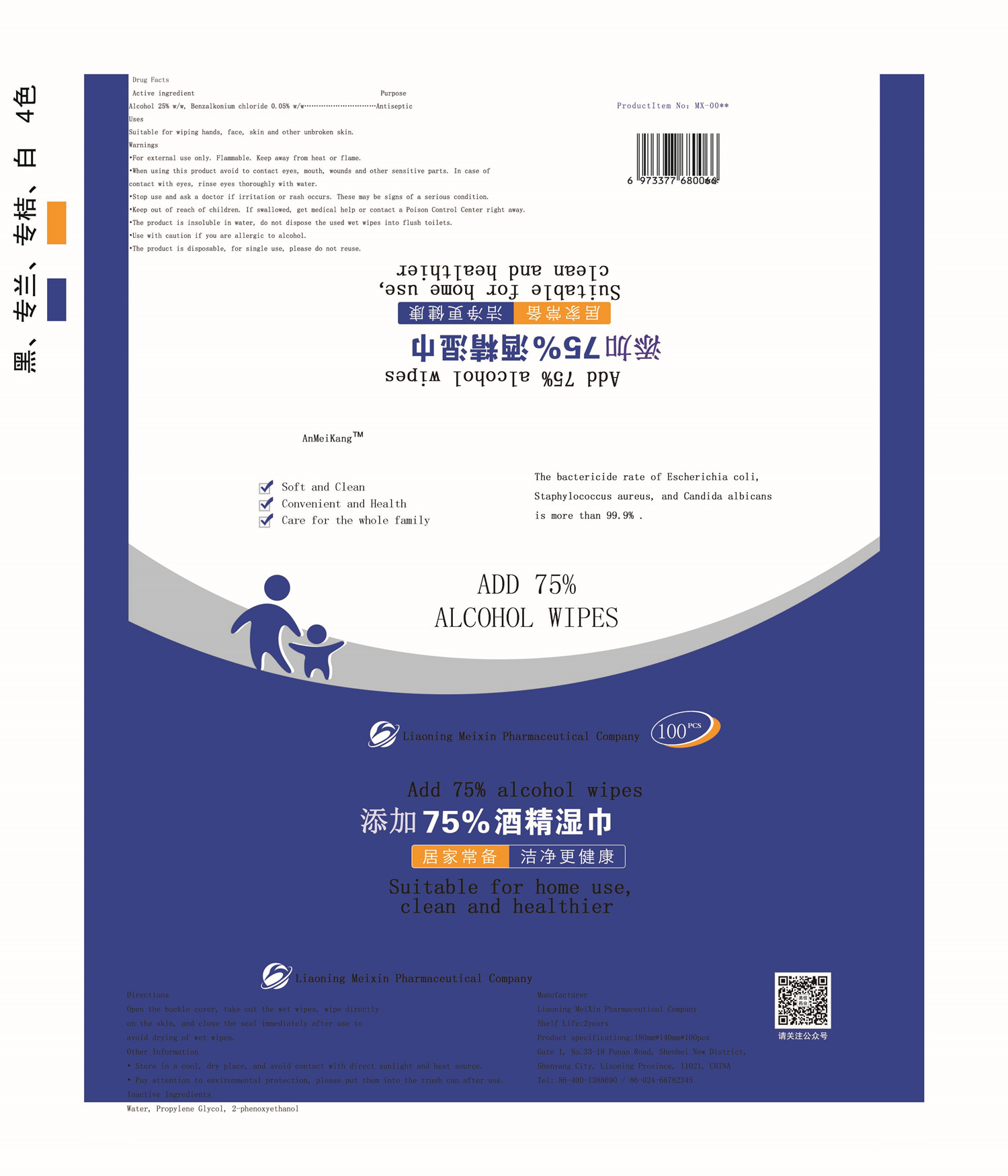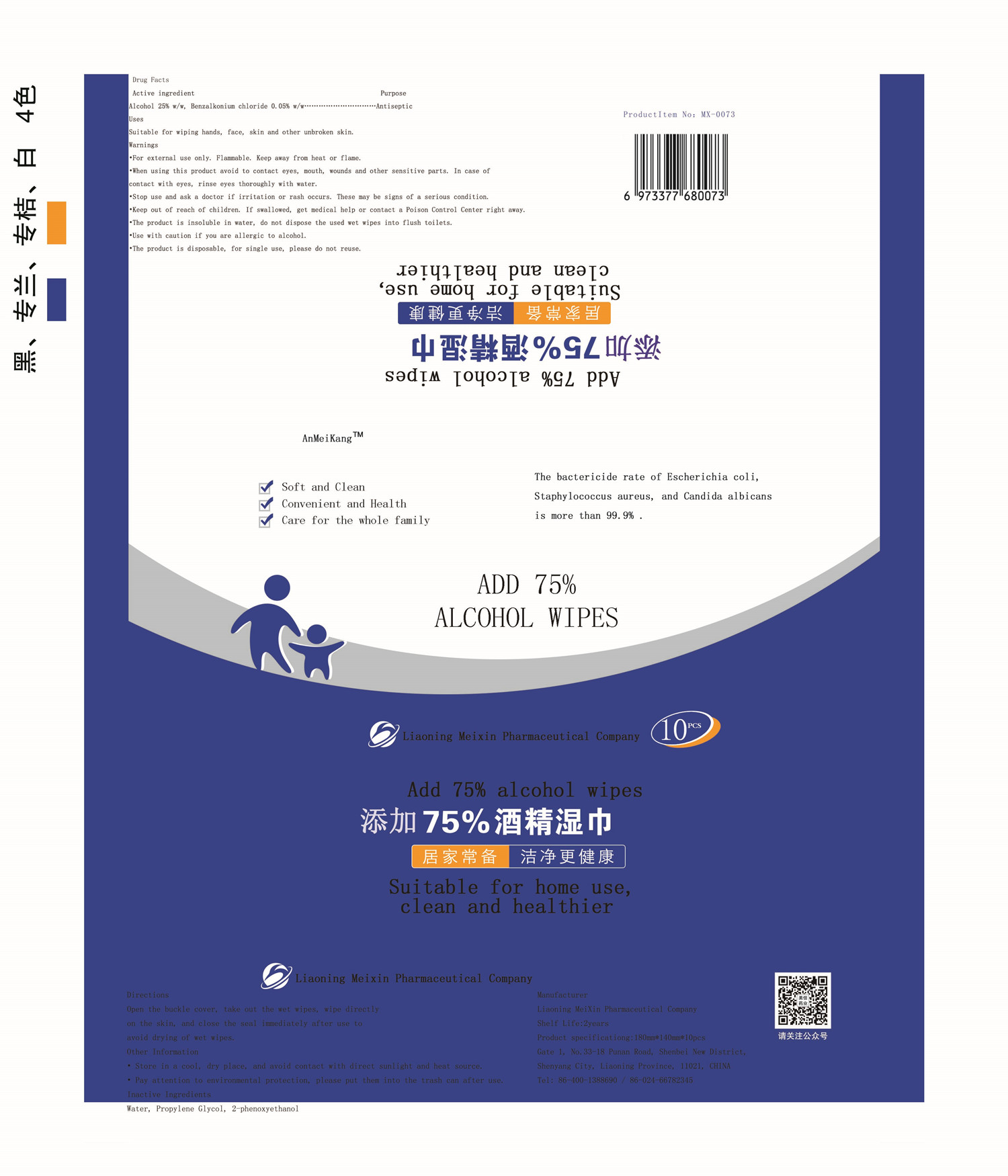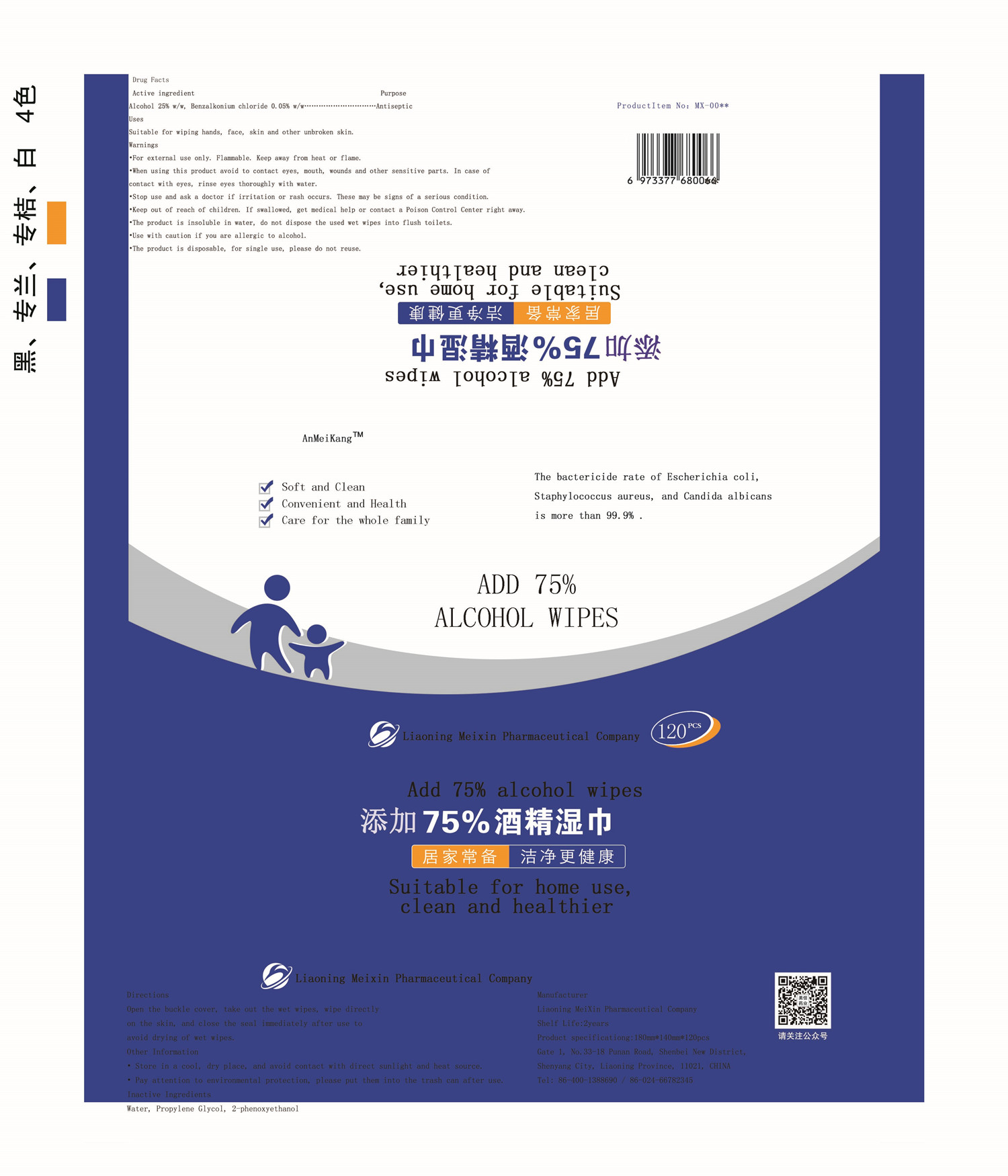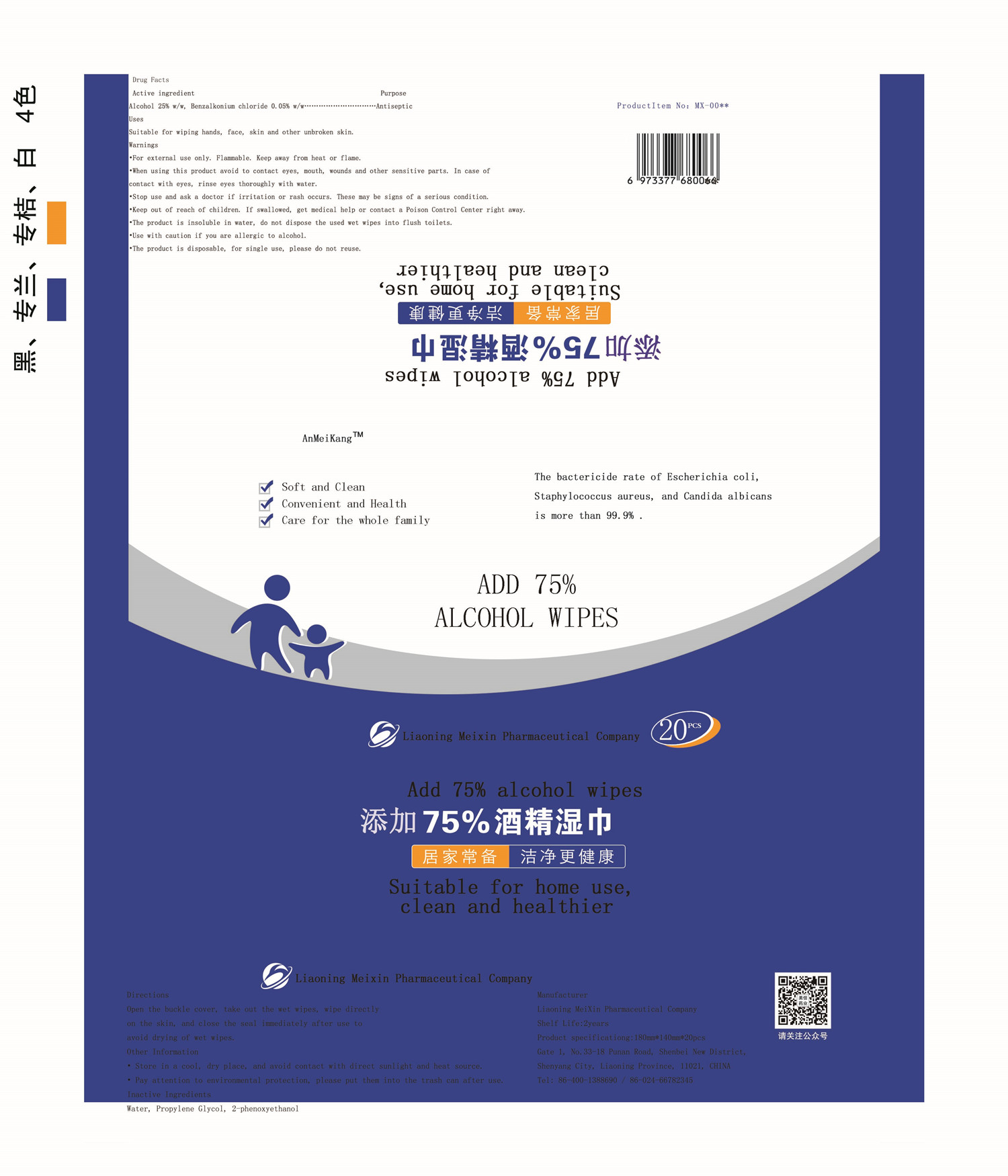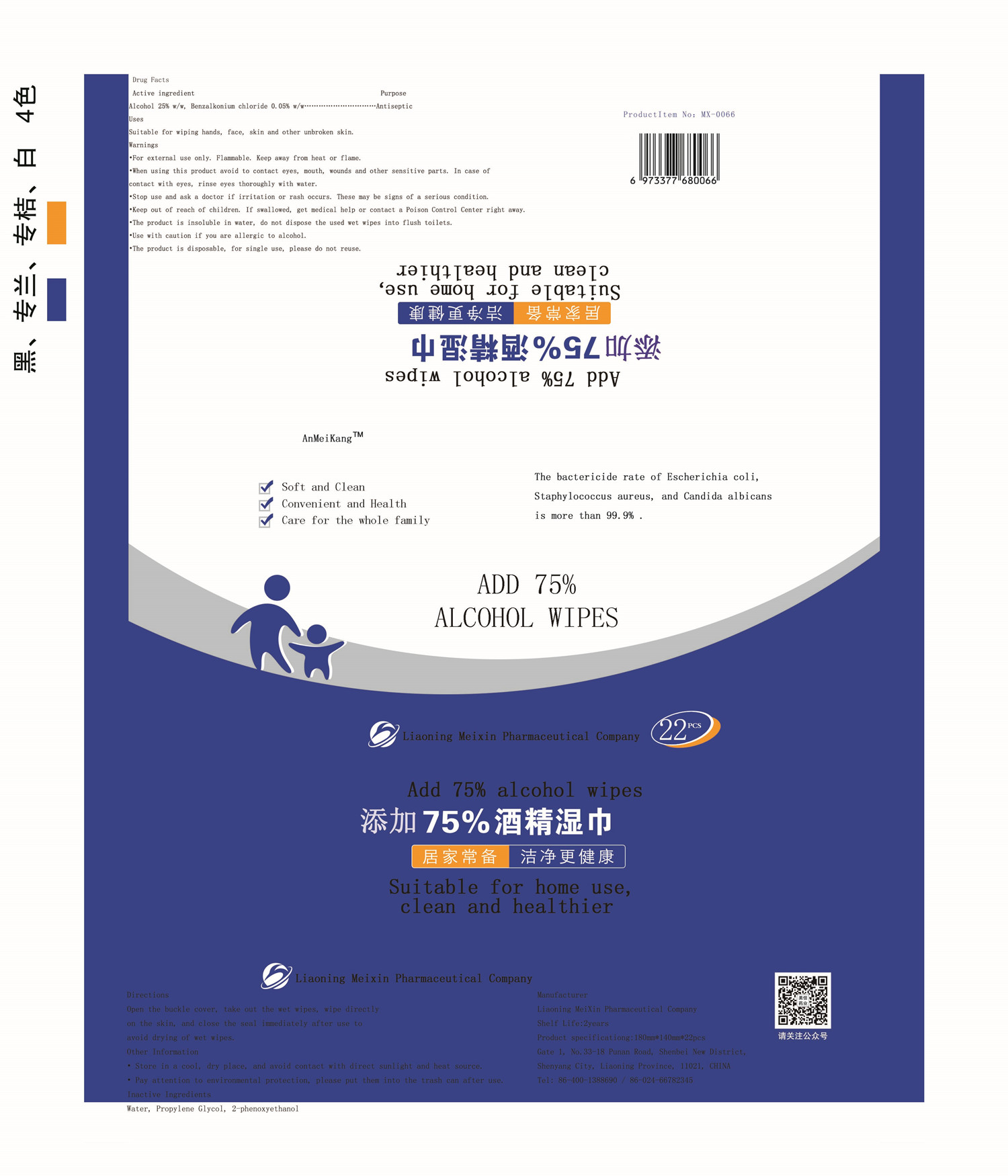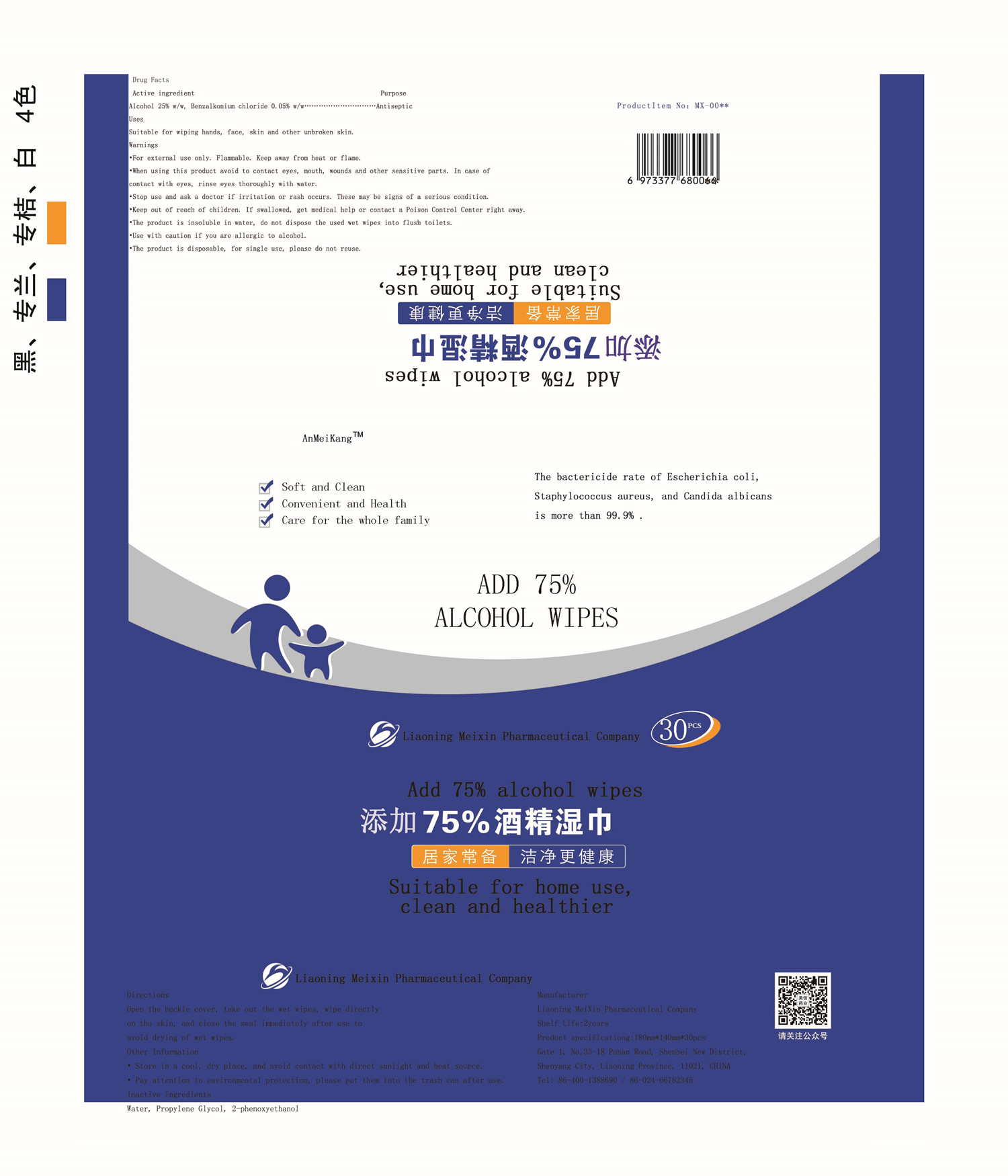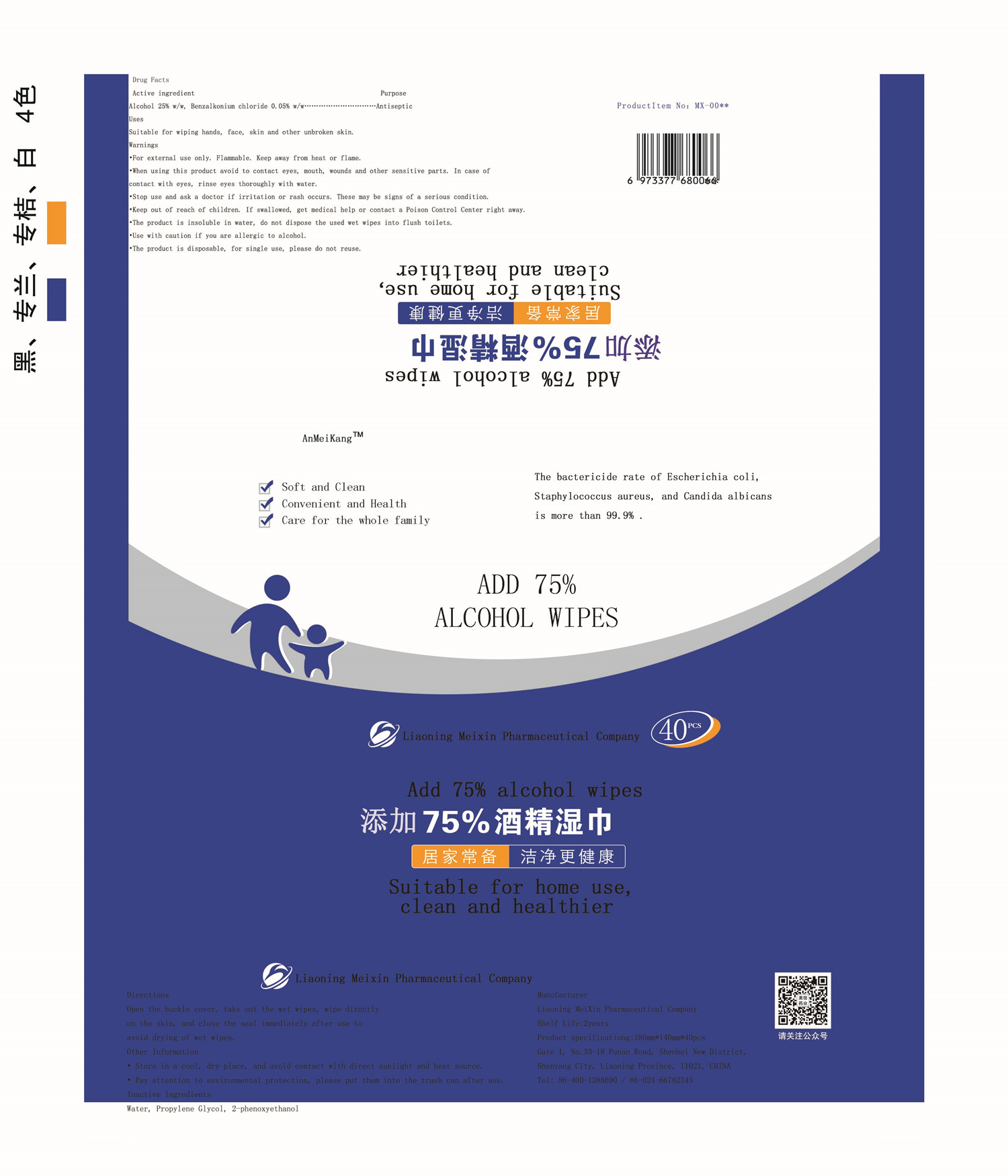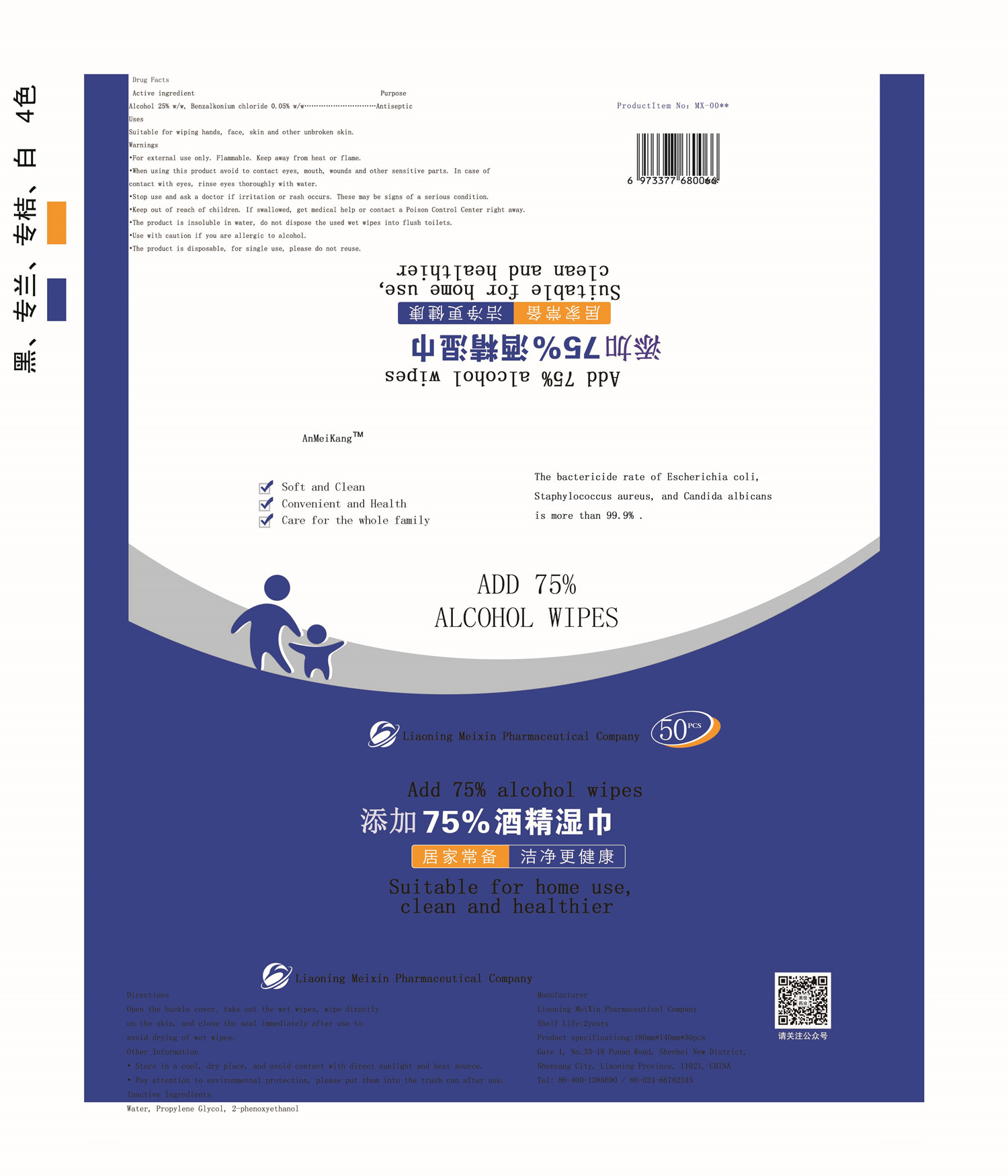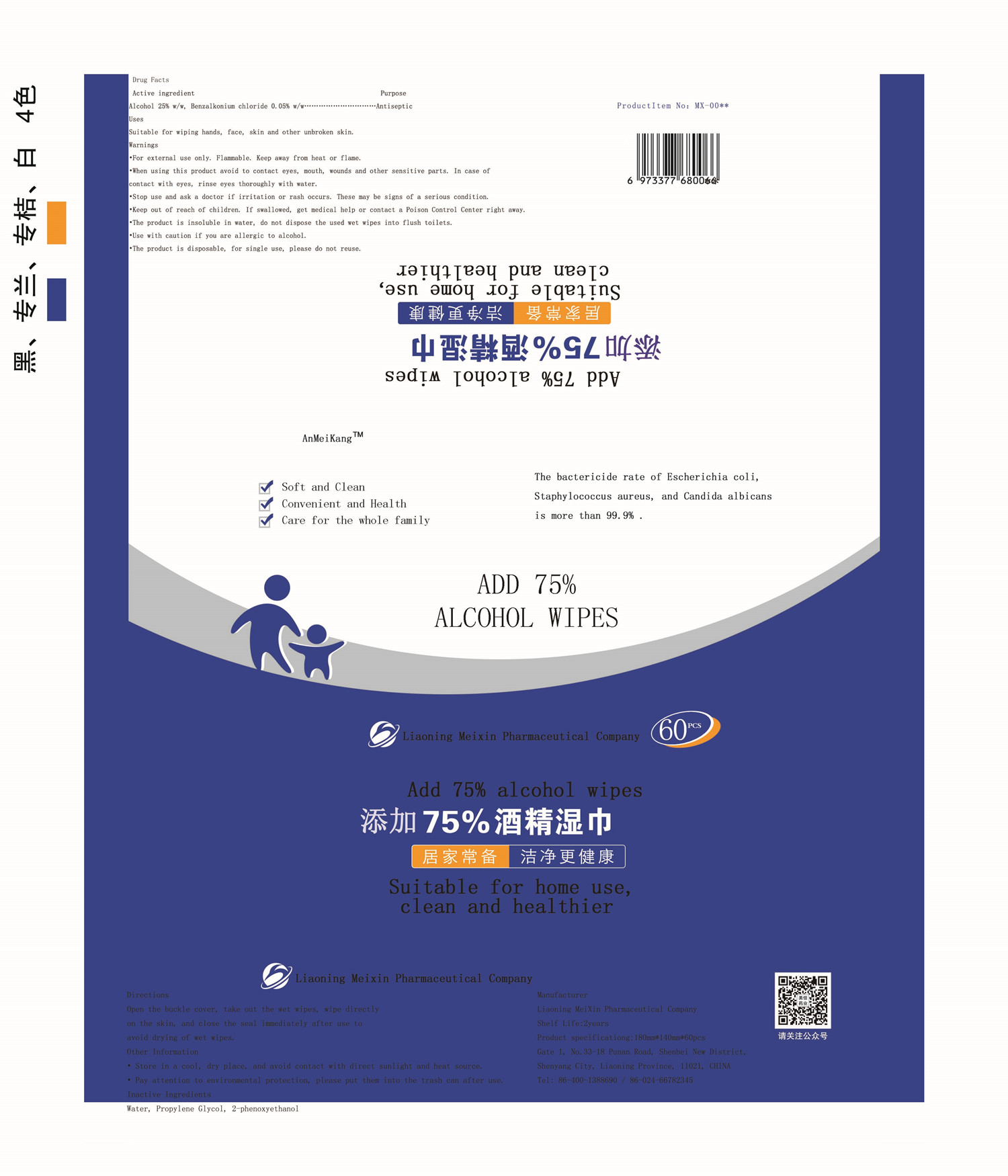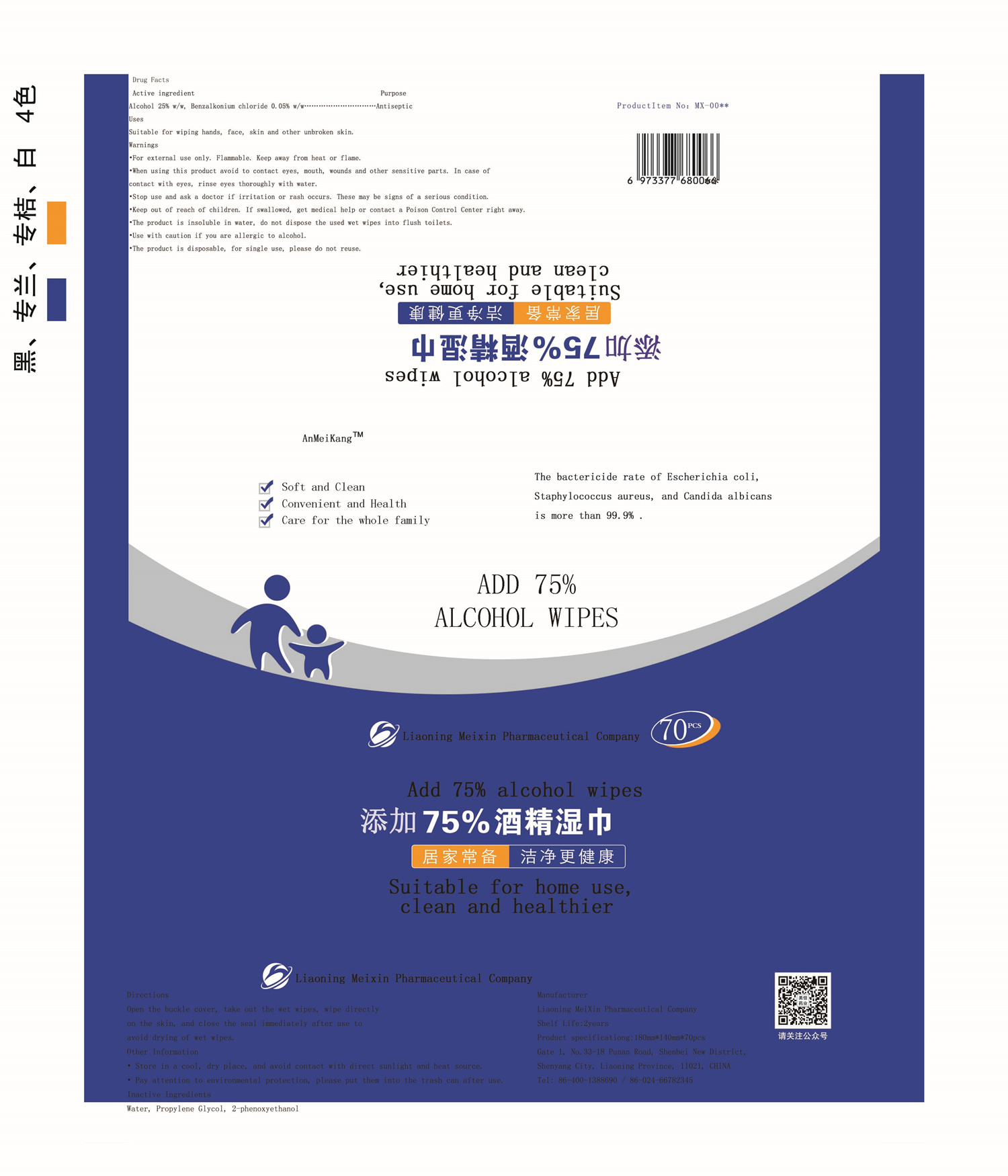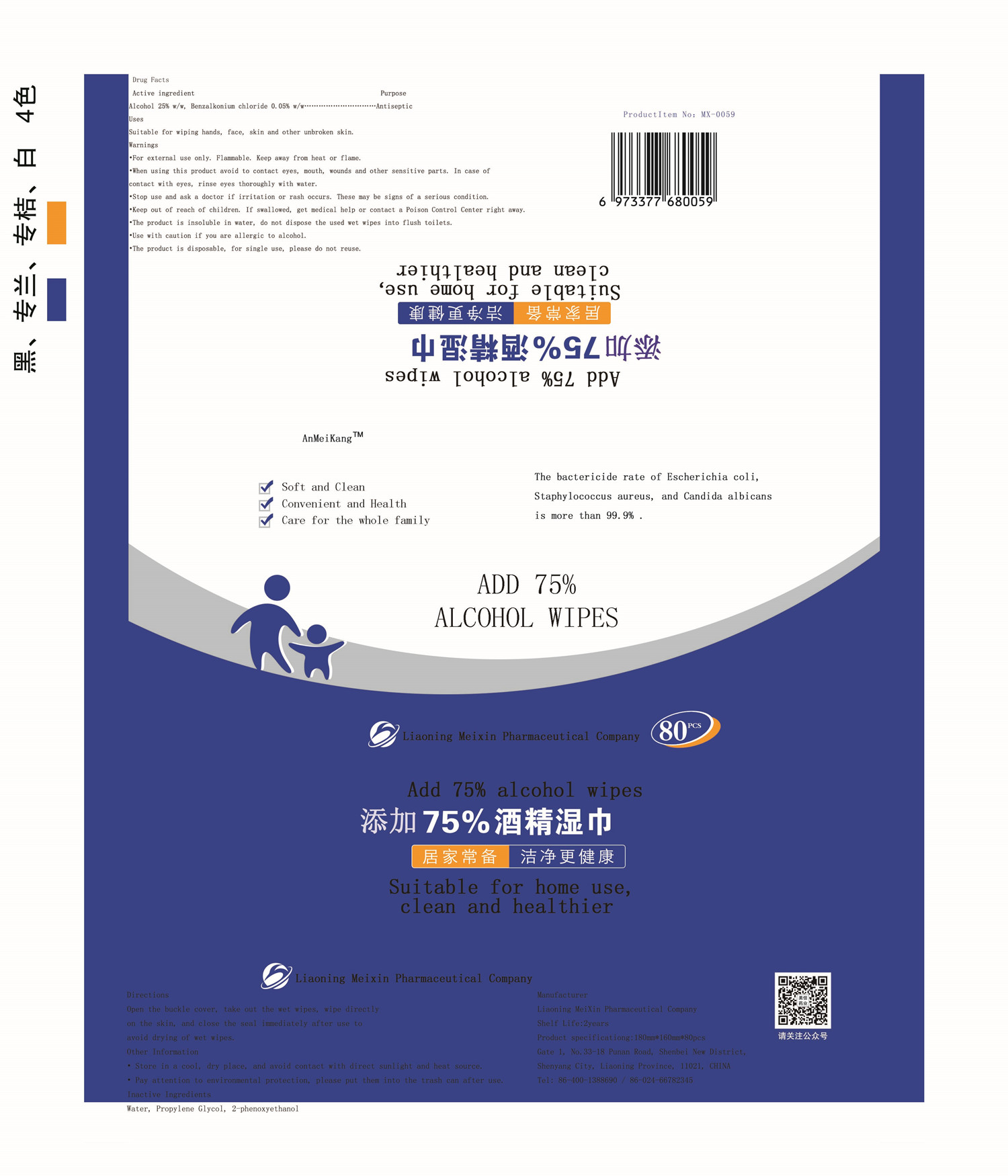 DRUG LABEL: AnMeiKang Alcohol Wipes
NDC: 81496-001 | Form: CLOTH
Manufacturer: Liaoning MeiXin Pharmaceutical Company
Category: otc | Type: HUMAN OTC DRUG LABEL
Date: 20210308

ACTIVE INGREDIENTS: ALCOHOL 0.8372 g/1 1; BENZALKONIUM CHLORIDE 0.005875 g/1 1
INACTIVE INGREDIENTS: PHENOXYETHANOL; WATER; PROPYLENE GLYCOL

AnMeiKang Alcohol Wipes

Active ingredient

Alcohol 25% w/w, Benzalkonium chloride 0.05% w/w

Purpose

Antiseptic

Uses

Suitable for wiping hands, face, skin and other unbroken skin.

Warnings

For external use only. Flammable. Keep away from heat or flame.

When using this product avoid to contact eyes, mouth, wounds and other sensitive parts. In case of contact with eyes, rinse eyes thoroughly with water.

Stop use and ask a doctor if irritation or rash occurs. These may be signs of a serious condition.

Keep out of reach of children. If swallowed, get medical help or contact a Poison Control Center right away.

The product is insoluble in water, do not dispose the used wet wipes into flush toilets.

Use with caution if you are allergic to alcohol.

The product is disposable, for single use, please do not reuse.

When using this product avoid to contact eyes, mouth, wounds and other sensitive parts. In case of contact with eyes, rinse eyes thoroughly with water.

Stop use and ask a doctor if irritation or rash occurs. These may be signs of a serious condition.

Directions

Open the buckle cover, take out the wet wipes, wipe directly on the skin, and close the seal immediately after use to avoid drying of wet wipes.

Keep out of reach of children. If swallowed, get medical help or contact a Poison Control Center right away.

Other Information

· Store in a cool, dry place, and avoid contact with direct sunlight and heat source.

· Pay attention to environmental protection, please put them into the trash can

Inactive Ingredients

Water, Propylene Glycol, 2-phenoxyethanol

PACKAGE LABEL

10PCS, NDC: 81496-001-01

PACKAGE LABEL

20PCS, NDC: 81496-001-02

PACKAGE LABEL

22PCS, NDC: 81496-001-03

PACKAGE LABEL

30PCS, NDC: 81496-001-04

PACKAGE LABEL

40PCS, NDC: 81496-001-05

PACKAGE LABEL

50PCS, NDC: 81486-001-06

PACKAGE LABEL

60PCS, NDC: 81496-001-07

PACKAGE LABEL

70PCS, NDC: 81496-001-08

PACKAGE LABEL

80PCS, NDC: 81496-001-09

PACKAGE LABEL

100PCS, NDC: 81496-001-10

PACKAGE LABEL

120PCS, NDC: 81496-001-11